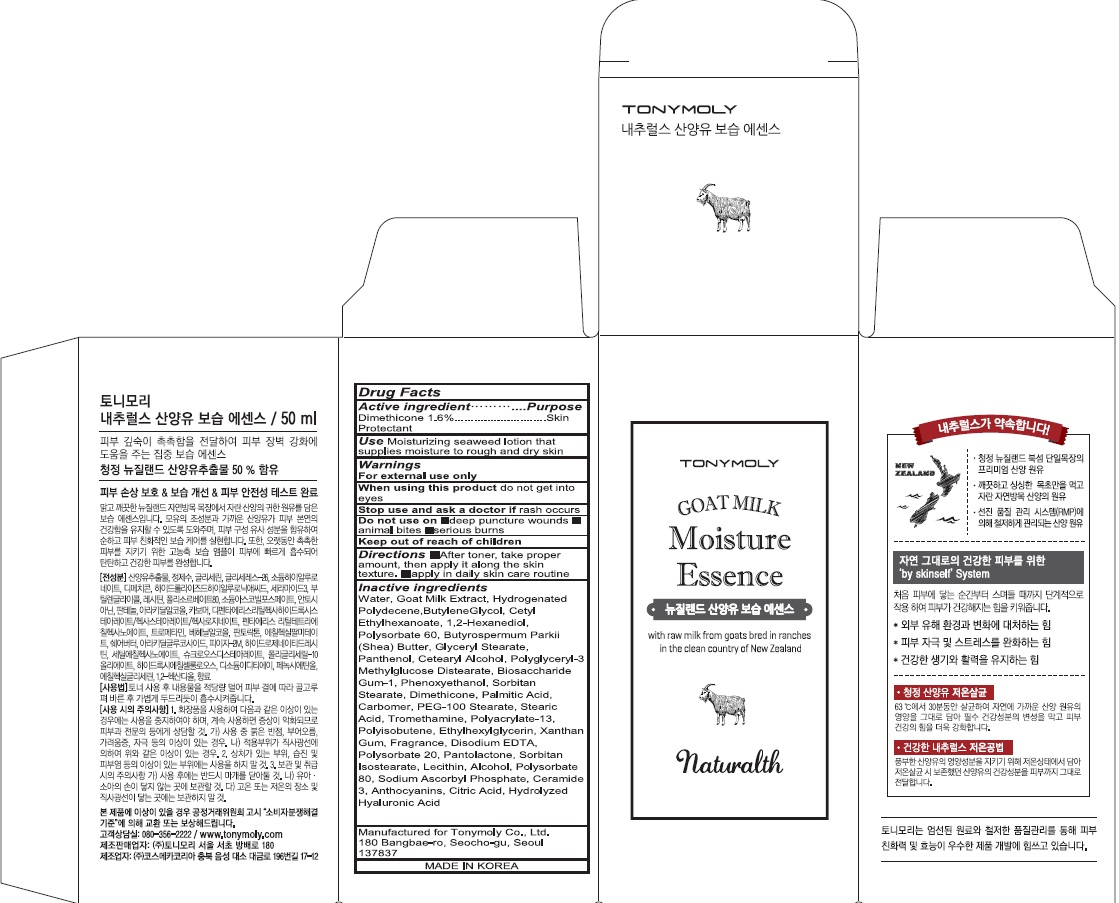 DRUG LABEL: NATURALTH GOAT MILK MOISTURE ESSENCE
NDC: 59078-290 | Form: CREAM
Manufacturer: TONYMOLY CO.,LTD
Category: otc | Type: HUMAN OTC DRUG LABEL
Date: 20160527

ACTIVE INGREDIENTS: Dimethicone 0.8 g/50 mL
INACTIVE INGREDIENTS: Water; Butylene Glycol

ACTIVE INGREDIENT

Active ingredient: Dimethicone 1.6%

INACTIVE INGREDIENT

Inactive Ingredient: Water, Goat Milk Extract, Hydrogenated Polydecene, Butylene Glycol, Cetyl Ethylhexanoate, 1,2-Hexanediol, Polysorbate 60, Butyrospermum Parkii (Shea) Butter, Glyceryl Stearate, Panthenol, Cetearyl Alcohol, Polyglyceryl-3 Methylglucose Distearate, Biosaccharide Gum-1, Phenoxyethanol, Sorbitan Stearate, Dimethicone, Palmitic Acid, Carbomer, PEG-100 Stearate, Stearic Acid, Tromethamine, Polyacrylate-13, Polyisobutene, Ethylhexylglycerin, Xanthan Gum, Fragrance, Disodium EDTA, Polysorbate 20, Pantolactone, Sorbitan Isostearate, Lecithin, Alcohol, Polysorbate 80, Sodium Ascorbyl Phosphate, Ceramide 3, Anthocyanins, Citric Acid, Hydrolyzed Hyaluronic Acid

PURPOSE

Purpose: Skin Protectant

WARNINGS

Warnings: For external use only. When using this product do not get into eyes. Stop use and ask a doctor if rash occurs. Do not use on - deep puncture wounds - animal bites - serious burns Keep out of reach of children.

KEEP OUT OF REACH OF CHILDREN

Use

Use: Moisturizing seaweed lotion that supplies moisture to rough and dry skin

Directions

Directions: - After toner, take proper amount, then apply it along the skin texture. - apply in daily skin care routine